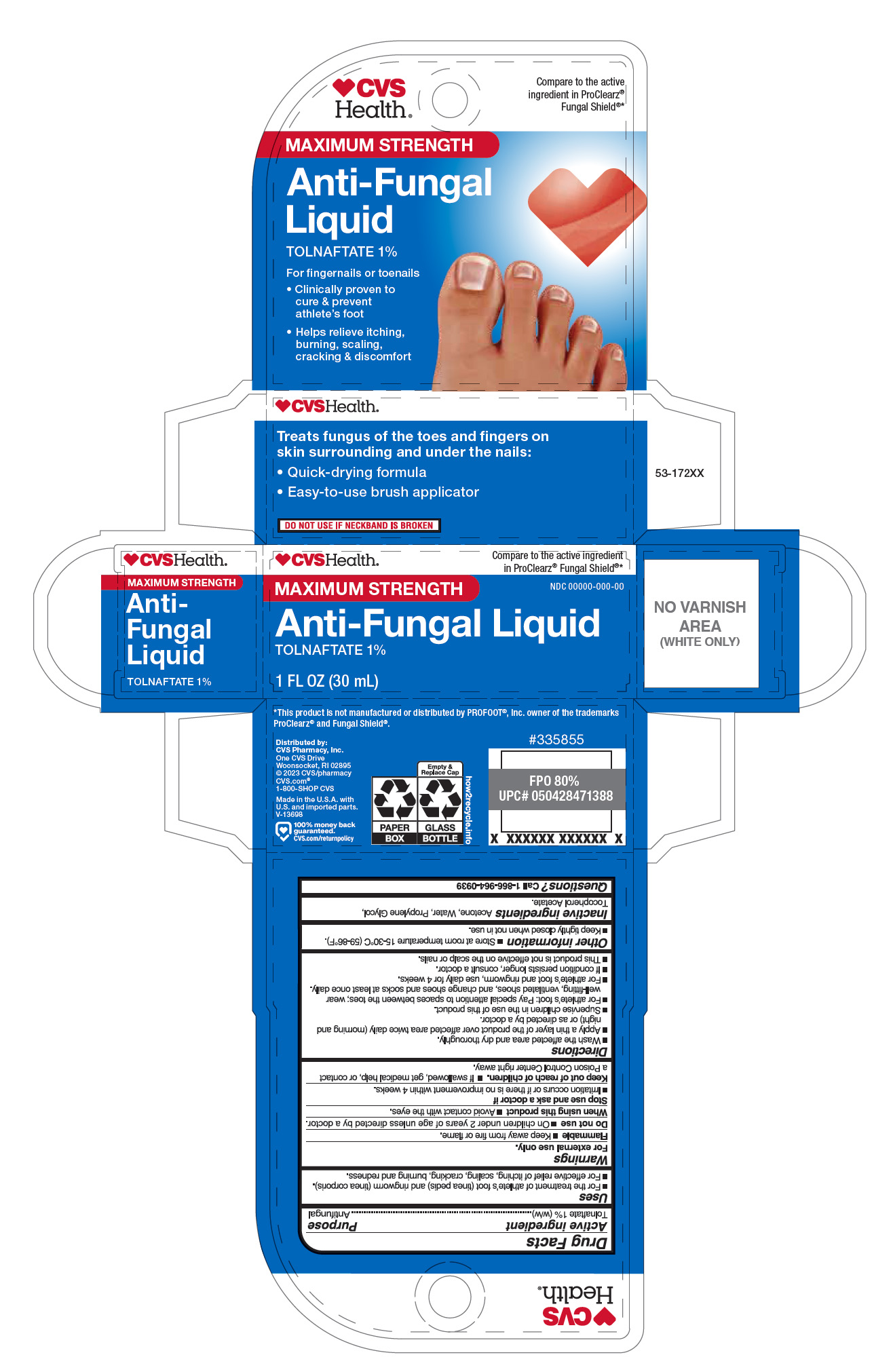 DRUG LABEL: Maximum Strength Antifungal Liquid
NDC: 51316-898 | Form: LIQUID
Manufacturer: CVS Pharmacy
Category: otc | Type: HUMAN OTC DRUG LABEL
Date: 20251029

ACTIVE INGREDIENTS: TOLNAFTATE 0.3 g/30 mL
INACTIVE INGREDIENTS: WATER; TOCOPHEROL; ACETONE; PROPYLENE GLYCOL

CVS Health Tolnaftate 1% Maximum Strength Anti-Fungal Liquid

Active ingredient

Tolnaftate 1% w/w

Purpose

Antifungal

Uses

- For the treament of athlete's foot (tinea pedis) and ring worm (tinea corporis).
- For effective relief of itching, scaling, cracking, burning, and redness.

Warnings

For external use only.

Do not use

on children under 2 years of age unless directed by a doctor.

When using this product

avoid contact with eyes.

Stop use and consult a doctor if

- irritation occurs or if there is no improvement in 4 weeks.

Keep out of reach of children.

If swallowed, get medical help or contact a Poison Control Center right away.

Flammable

- Keep away from fire or flame.

Directions

- wash the affected area and dry thoroughly.
- apply a thin layer of the product over the affected area twice daily (morning and night) or as directed by a doctor.
- supervise children in the use of this product.
- for athlete's foot: pay special attention to spaces between toes; wear well-fitting, ventilated shoes, and change shoes and socks at least once daily.
- for athlete's foot and ringworm, use daily for 4 weeks.
- If condition persists longer, consult a doctor.
- this product is not effective on the scalp or nails.

Other information

- store at room temperature 15°-30°C (59° - 86°F).
- keep tightly closed when not in use.

Inactive ingredient

Acetone, Water, Propylene Glycol, Tocopherol Acetate.

Questions?

Call 1-866-964-0939

Principal Display Panel

maximum

strength

antifungal

liquid

tolnaftate 1%

For fingernails or townails

Clinically proven to cure and prevent athelete's foot

Helps relieve itching, burning, scaling, cracking & discomfort

Treats Fungus of the toes and fingers on skin surrounding and under the nails

Quick drying formula

Easy to apply brush applicator

NET 1 FL OZ (30 mL)